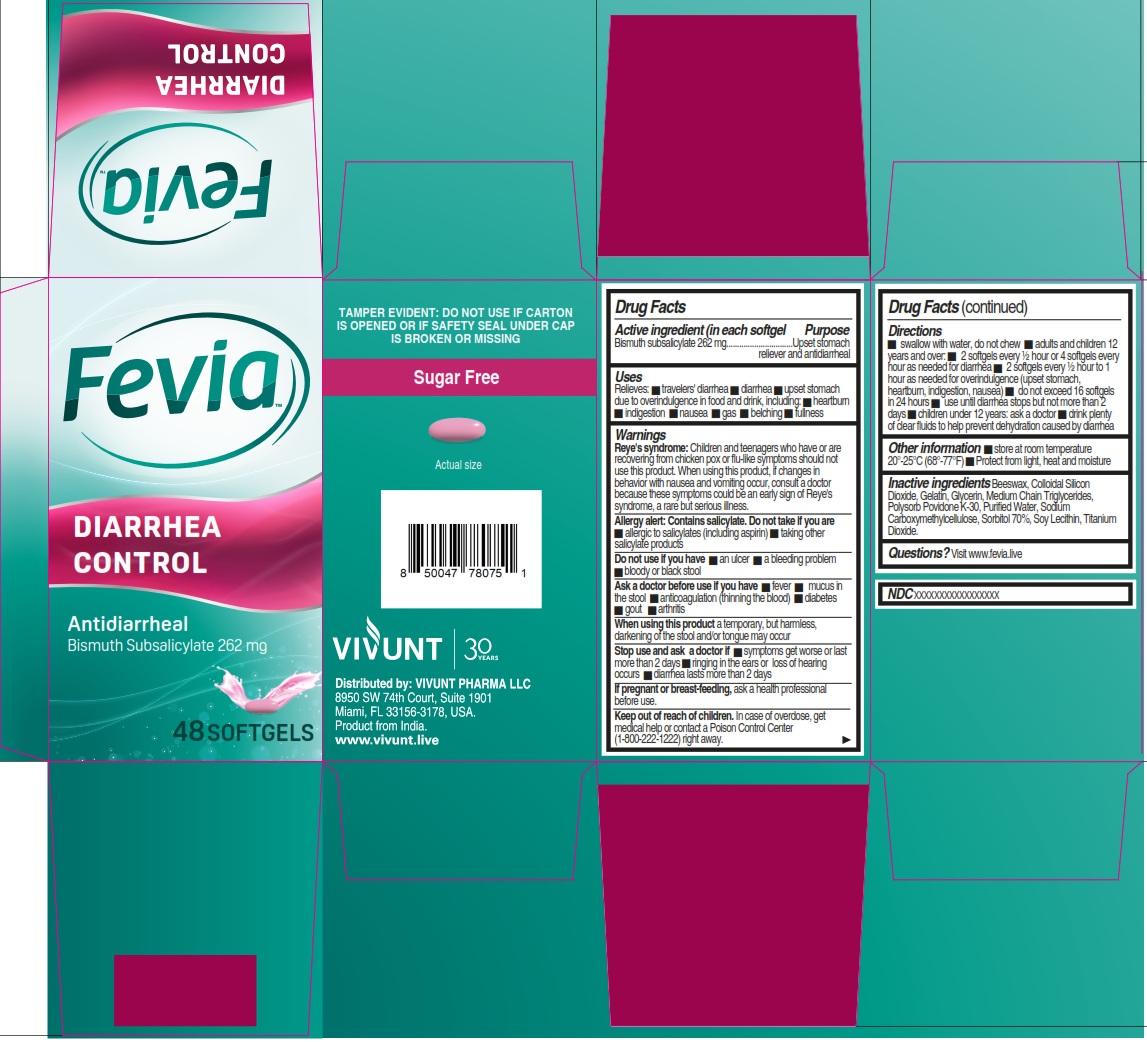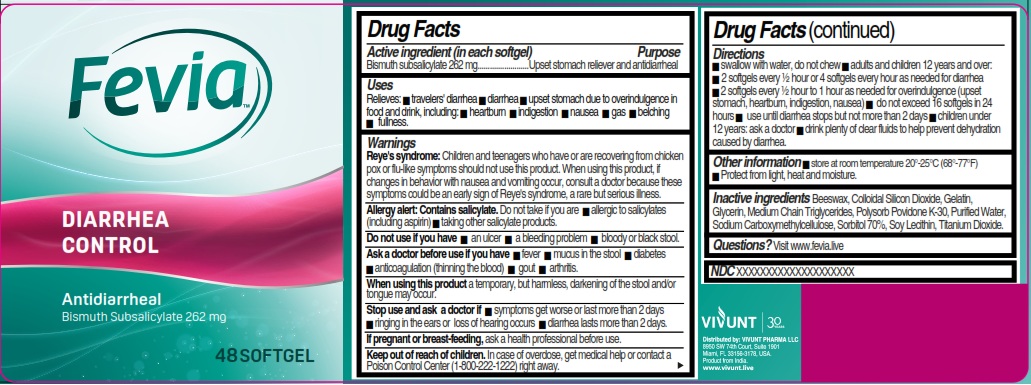 DRUG LABEL: FEVIA Diarrhea Control
NDC: 82706-028 | Form: CAPSULE, LIQUID FILLED
Manufacturer: VIVUNT PHARMA LLC
Category: otc | Type: HUMAN OTC DRUG LABEL
Date: 20260226

ACTIVE INGREDIENTS: BISMUTH SUBSALICYLATE 262 mg/1 1
INACTIVE INGREDIENTS: GLYCERIN; SOYBEAN LECITHIN; TITANIUM DIOXIDE; SILICON DIOXIDE; POVIDONE K30; BEESWAX; GELATIN; CARBOXYMETHYLCELLULOSE SODIUM; SORBITOL SOLUTION 70%; MEDIUM-CHAIN TRIGLYCERIDES; WATER

FEVIA Diarrhea control 48

Drug Facts

Active ingredient (in each softgel)

Bismuth subsalicylate 262 mg

Purpose

Upset stomach reliever and antidiarrheal

Uses

Relieves:

- traveler´s diarrhea
- diarrhea
- upset stomach due to overindulgence in food and drink, including:
- heartburn
- indigestion
- nausea
- gas
- belching
- fullness

Warnings

Reye´s syndrome: Children and teenagers who have or are recovering from chicken pox or flu-like symptoms should not use this product. When using this product, if changes in behaviour with nausea and vomiting occur, consult a doctor because these symptoms could be an early sign of Reye´s syndrome, a rare but serious illness.

Allergy alert: Contains salicylate. Do not take if you are

- allergic to salicylates (including aspirin)
- taking other salicylate products

Do not use if you have

- an ulcer
- a bleeding problem
- bloody or block stool

Ask a doctor before use if you have

- fever
- mucus in the stool
- anticoagulation (thinning the blood)
- diabetes
- gout
- arthritis

When using this product

a temporary, but harmless, darkening of the stool and/or tongue may occur

Stop use and ask a doctor if

- symptoms get worse or last more than 2 days
- ringing in the ears or loss of hearing occurs
- diarrhea lasts more than 2 days

If pregnant or breast-feeding,

ask a health professional before use.

Keep out of reach of children. In case of overdose, get medical help or contact a Poison Control Center (1-800-222-1222) right away.

Directions

- swallow with water, do not chew
- adults and children 12 years and over:
- 2 softgels every 1/2 hour or 4 softgels every hour as needed for diarrhea
- 2 softgels every 1/2 hour to 1 hour as needed for overindulgence (upset stomach, heartburn, indigestion, nausea)
- do not exceed 16 softgels in 24 hours
- use until diarrhea stops but no more than 2 days
- children under 12 years: ask a doctor
- drink plenty of clear fluids to help revent dehydration caused by diarrhea

Other information

- store at room temperature 20°-25°C (68°-77°F)
- Protect from light, heat and moisture

Inactive ingredients

Beeswax, Colloidal Silicon Dioxide, Gelatin, Glycerin, Medium Chain Triglycerides, Polysorb, Povidone K-30, Purified Water, Sodium Carboxymethylcellulose, Sorbitol 70%, Soy Lechitin, Titanium Dioxide.

Questions?

Visit www.fevia.live

Distributed by

VIVUNT

Distributed by: VIVUNT PHARMA LLC

8950 SW 74th Court, Suite 1901

Miami, FL 33156-3178, USA.

Product from India.

www.vivunt.live

PACKAGE LABEL

Fevia™

DIARRHEA CONTROL

Antidiarrheal

Bismuth Subsalicylate 262 mg

48 SOFTGELS

TAMPER EVIDENT: DO NOT USE IF CARTON IS OPENED OR IF SAFETY SEAL UNDER CAP IS BROKEN OR MISSING

Sugar Free

Actual size